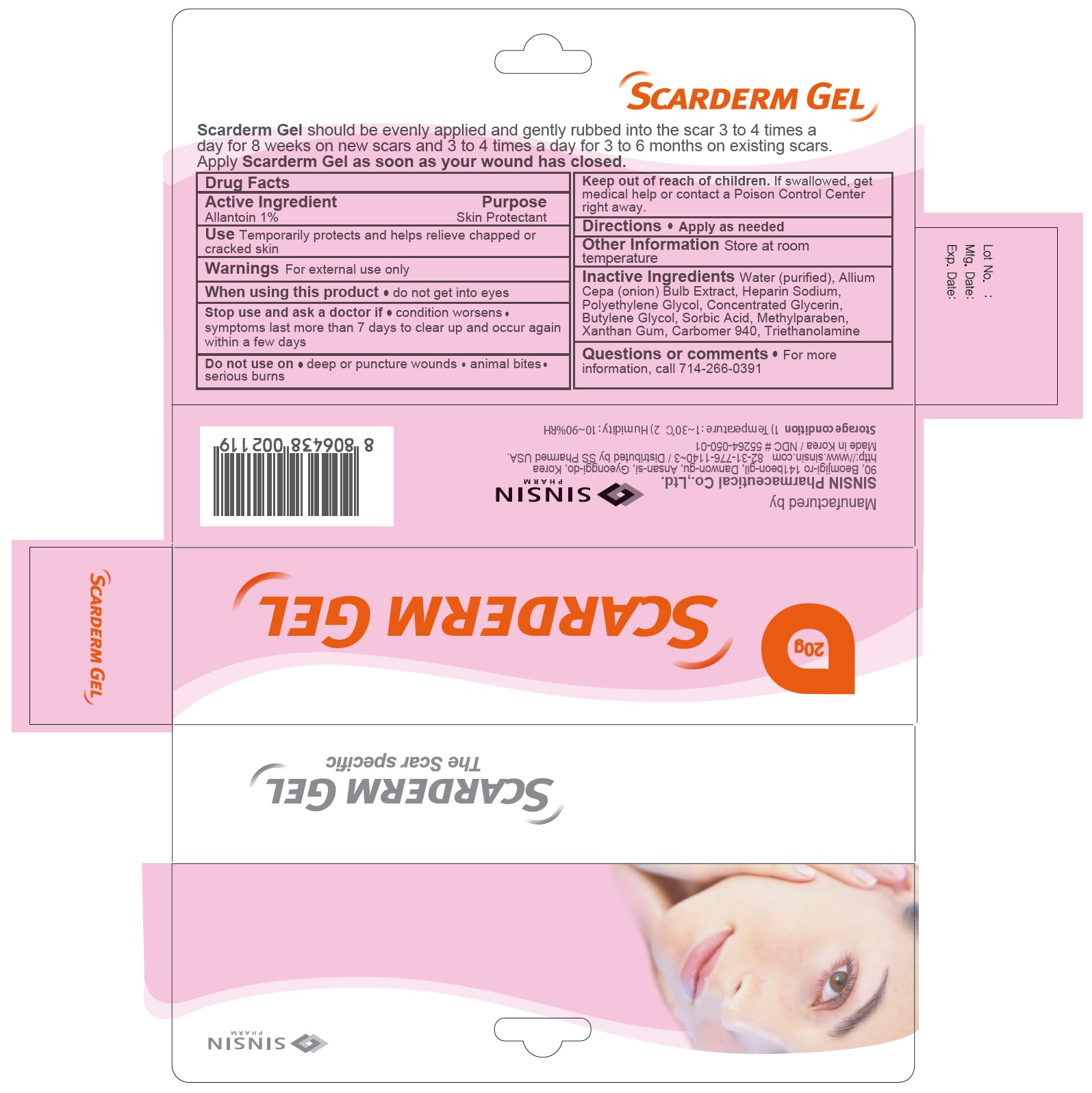 DRUG LABEL: Scarderm
NDC: 55264-050 | Form: GEL
Manufacturer: Sinsin Pharmaceutical Co., Ltd.
Category: otc | Type: HUMAN OTC DRUG LABEL
Date: 20160530

ACTIVE INGREDIENTS: Allantoin 10 mg/1 g
INACTIVE INGREDIENTS: Water; Onion; Heparin Sodium; Polyethylene Glycol 400; Glycerin; Butylene Glycol; Sorbic Acid; Methylparaben; Xanthan Gum; Panthenol; CARBOMER HOMOPOLYMER TYPE C (ALLYL PENTAERYTHRITOL CROSSLINKED); Trolamine

Scarderm

Drug Facts

Active Ingredient

Allantoin 1%

Purpose

Skin Protectant

Use

Temporatrily protects and helps relieve chapped or cracked skin

Warnings

For external use only

When using this product do not get into eyes

Stop use and ask a doctor if

- condition worsens
- symptoms last more than 7 days or clear up and occur again within a few days

Do not use on

- deep or puncture wounds
- animal bites
- serious burns

Keep out of reach of children. If swallowed, get medical help or contact a Poison Control Center right away.

Directions

Apply as needed.

Other information

Store at room temperature

Inactive Ingredients

Water (purified), Allium Cepa (Onion) Bulb Extract, Heparin Sodium, Polyethylene Glycol, Concentrated Glycerin, Butylene Glycol, Sorbic Acid, Methylparaben, Jantangeom, Carbomer 940, Triethanolamine

Questions or Comments?

For more information call 714-266-0391